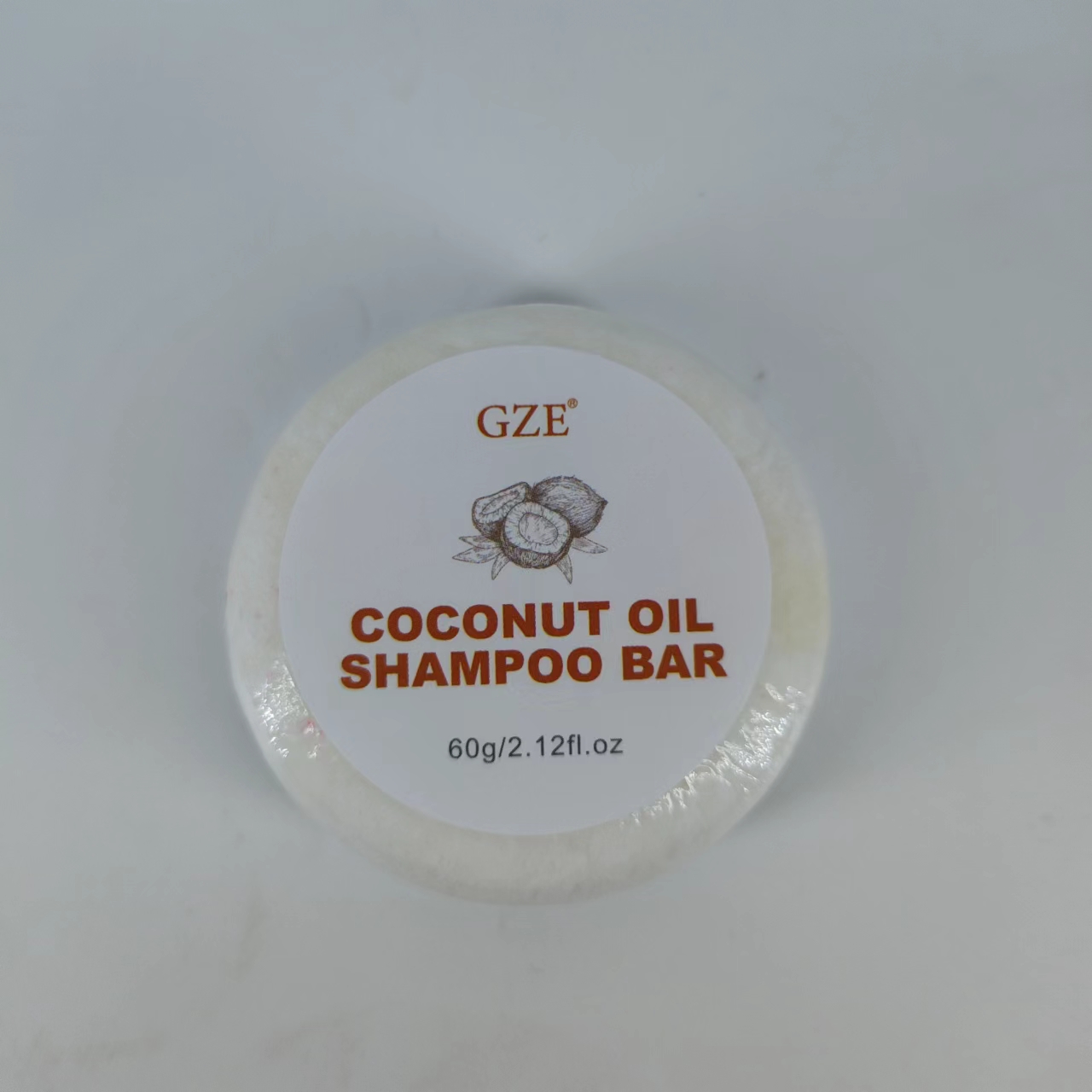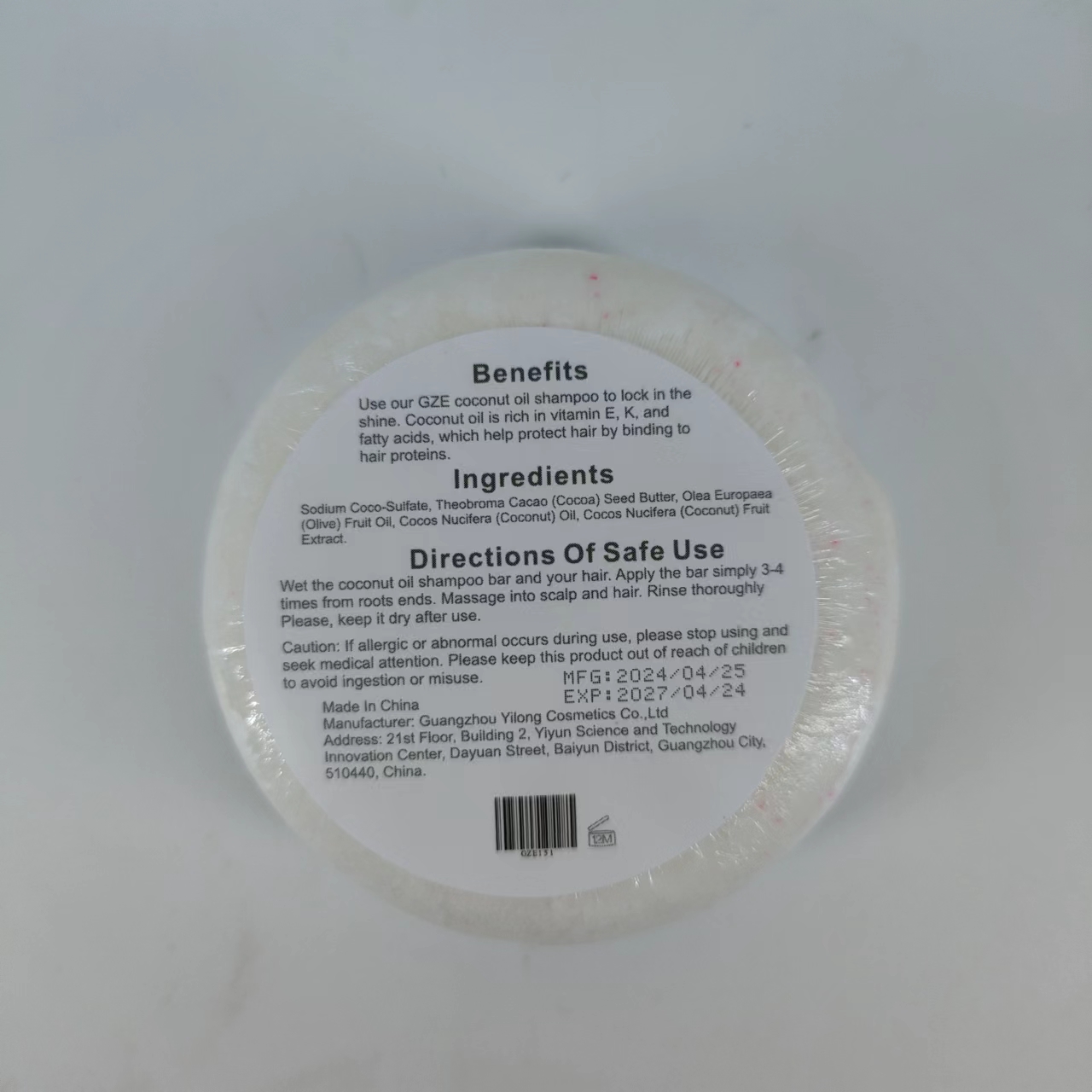 DRUG LABEL: GZE Coconut Oil ShampooBar
NDC: 83566-151 | Form: SOAP
Manufacturer: Guangzhou Yilong Cosmetics Co., Ltd
Category: otc | Type: HUMAN OTC DRUG LABEL
Date: 20240612

ACTIVE INGREDIENTS: COCOS NUCIFERA WHOLE 15 g/60 g; COCONUT OIL 15 g/60 g; OLIVE OIL 10 g/60 g; COCOA BUTTER 10 g/60 g
INACTIVE INGREDIENTS: SODIUM COCO-SULFATE

GZE coconut oil shampoo bar

ACTIVE INGREDIENT

COCOS NUCIFERA WHOLE
COCOA BUTTER
OLIVE OIL
COCONUT OIL

PURPOSE

Clean hair.

INDICATIONS AND USAGE

Wet the coconut oil shampoo bar and your hair. Apply the bar simply 3-4 times from roots ends. Massage into scalp and hair, Rinse thoroughly Please, keep it dry after use.

WARNINGS

For external use only.

Stop use and ask a doctor if rash occurs.

Do not use on damaged or broken skin.

When using this product keep out of eyes. Rinse with water to remove.

Keep out of reach of children. If swallowed, get medical help or contact a Poison Control Center right away.

DOSAGE AND ADMINISTRATION

Wet the coconut oil shampoo bar and your hair. Apply the bar simply 3-4 times from roots ends. Massage into scalp and hair, Rinse thoroughly Please, keep it dry after use.

INACTIVE INGREDIENT

SODIUM COCO-SULFATE